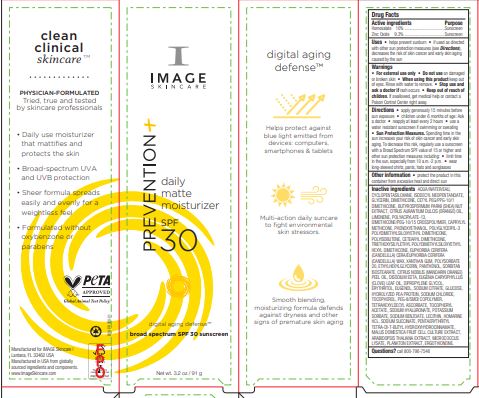 DRUG LABEL: Prevention Daily Matte Moisturizer SPF 30
NDC: 62742-4223 | Form: CREAM
Manufacturer: Allure Labs
Category: otc | Type: HUMAN OTC DRUG LABEL
Date: 20241209

ACTIVE INGREDIENTS: ZINC OXIDE 9.3 g/100 g; HOMOSALATE 10 g/100 g
INACTIVE INGREDIENTS: APPLE PEEL; ARABIDOPSIS THALIANA; CLOVE LEAF OIL; ERGOTHIONEINE; PHENOXYETHANOL; SODIUM CITRATE; AMMONIUM ACRYLOYL DIMETHYLTAURATE/METHACRYLATE, DIMETHYLACRYLAMIDE AND METHACRYLIC ACID COPOLYMER, PPG-3 GLYCERYL TRIACRYLATE CROSSLINKED (100000 MW); DIMETHICONE/PEG-10/15 CROSSPOLYMER; CAPRYLYL TRISILOXANE; ETHYLHEXYLGLYCERIN; CANDELILLA WAX; ANHYDROUS DEXTROSE; TRIETHOXYSILYLETHYL POLYDIMETHYLSILOXYETHYL HEXYL DIMETHICONE; GLYCERIN; XANTHAN GUM; EDETATE DISODIUM ANHYDROUS; EUGENOL; SHEANUT; POLYGLYCERYL-3 POLYDIMETHYLSILOXYETHYL DIMETHICONE (4000 MPA.S); ISODECYL NEOPENTANOATE; TETRAHEXYLDECYL ASCORBATE; HYALURONATE SODIUM; .ALPHA.-TOCOPHEROL ACETATE; LECITHIN, SOYBEAN; SODIUM CHLORIDE; PEG-8/SMDI COPOLYMER; HOMARINE HYDROCHLORIDE; SODIUM SUCCINATE ANHYDROUS; P-METHYLAMINOPHENOL SULFATE; DIMETHICONE; CETYL PEG/PPG-10/1 DIMETHICONE (HLB 4); POLYISOBUTYLENE (55000 MW); POLYSORBATE 20; PANTHENOL; SORBITAN ISOSTEARATE; MANDARIN OIL; DIPROPYLENE GLYCOL; TOCOPHEROL; SODIUM BENZOATE; PENTAERYTHRITOL TETRAKIS(3-(3,5-DI-TERT-BUTYL-4-HYDROXYPHENYL)PROPIONATE); POTASSIUM SORBATE; ORANGE OIL; MICROCOCCUS LUTEUS; WATER; CYCLOMETHICONE 5; LIMONENE, (+)-; CETEARYL METHICONE (15000 MW); ERYTHRITOL; PEA PROTEIN

Drug Facts

Active ingredients

Homosalate 10%

Zinc Oxide 9.3%

Purpose:

Sunscreen

INDICATIONS AND USAGE

Uses • Helps prevent sunburn • if used as directed with other sun protection measures (see Directions), decreases the risk of skin cancer and early skin aging caused by the sun

Warnings :

For external use only

Do not use on damaged or broken skin

When using this product keep out of eyes. Rinse with water to remove

Stop use and ask a doctor if rash occurs

Keep out of reach of children. If swallowed, get medical help or contact a Poison Control Center right away

DOSAGE AND ADMINISTRATION

Directions • apply generously 15 minutes before sun exposure • children under 6 months of age: Ask a doctor • reapply at least every 2 hours • use a water resistant sunscreen if swimming or sweating

• Sun Protection Measures. Spending time in the sun increases your risk of skin cancer and early skin aging. To decrease this risk, regularly use a sunscreen with a Broad Spectrum SPF value of 15 or higher and other sun protection measures including: • limit time in the sun, especially from 10 a.m.-2 p.m. • wear long-sleeved shirts, pants, hats and sunglasses

Other information • protect the product in this container from excessive heat and direct sun

INACTIVE INGREDIENT

Inactive ingredients AQUA/WATER/EAU, CYCLOPENTASILOXANE, ISODECYL NEOPENTANOATE, GLYCERIN, DIMETHICONE, CETYL PEG/PPG-10/1 DIMETHICONE, BUTYROSPERMUM PARKII (SHEA) NUT EXTRACT, CITRUS AURANTIUM DULCIS (ORANGE) OIL, LIMONENE, POLYACRYLATE-13, DIMETHICONE/PEG-10/15 CROSSPOLYMER, CAPRYLYL METHICONE, PHENOXYETHANOL, POLYGLYCERYL-3 POLYDIMETHYLSILOXYETHYL DIMETHICONE, POLYISOBUTENE, CETEARYL DIMETHICONE, TRIETHOXYSILYLETHYL POLYDIMETHYLSILOXYETHYL HEXYL DIMETHICONE, EUPHORBIA CERIFERA (CANDELILLA) CERA/EUPHORBIA CERIFERA (CANDELILLA) WAX, XANTHAN GUM, POLYSORBATE 20, ETHYLHEXYLGLYCERIN, PANTHENOL, SORBITAN ISOSTEARATE, CITRUS NOBILIS (MANDARIN ORANGE) PEEL OIL, DISODIUM EDTA, EUGENIA CARYOPHYLLUS (CLOVE) LEAF OIL, DIPROPYLENE GLYCOL, ERYTHRITOL, EUGENOL, SODIUM CITRATE, GLUCOSE, HYDROLYZED PEA PROTEIN, SODIUM CHLORIDE, TOCOPHEROL, PEG-8/SMDI COPOLYMER, TETRAHEVLDECYL ASCORBATE, TOCOPHERYL ACETATE, SODIUM HYALURONATE, POTASSIUM SORBATE, SODIUM BENZOATE, LECITHIN, HOMARINE HCL, SODIUM SUCCINATE, PENTAERYTHRITYL TETRA-DI-T-BUTYL HYDROXYHYDROCINNAMATE, MALUS DOMESTICA FRUIT CELL CULTURE EXTRACT, ARABIDOPSIS THALIANA EXTRACT, MICROCOCCUS LYSATE, PLANKTON EXTRACT, ERGOTHIONEINE.